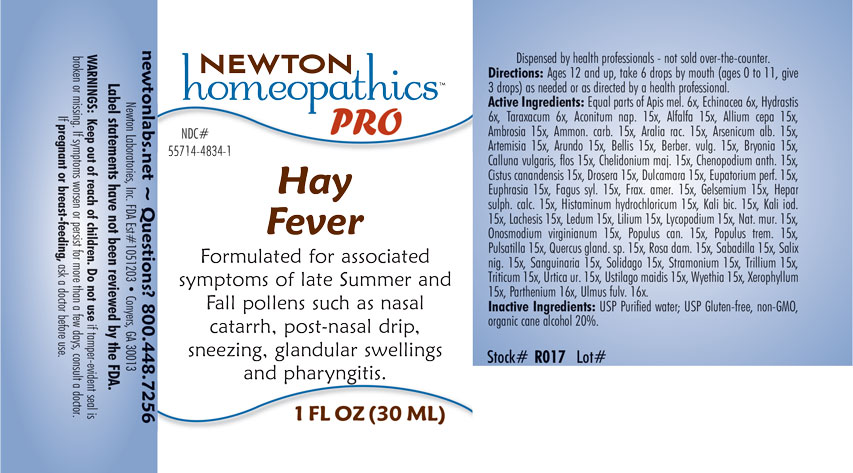 DRUG LABEL: Hay Fever
NDC: 55714-4834 | Form: LIQUID
Manufacturer: Newton Laboratories, Inc.
Category: homeopathic | Type: HUMAN OTC DRUG LABEL
Date: 20201203

ACTIVE INGREDIENTS: XEROPHYLLUM ASPHODELOIDES 15 [hp_X]/1 mL; SALIX NIGRA BARK 15 [hp_X]/1 mL; LILIUM LANCIFOLIUM WHOLE FLOWERING 15 [hp_X]/1 mL; ULMUS RUBRA BARK 16 [hp_X]/1 mL; FAGUS SYLVATICA NUT 15 [hp_X]/1 mL; ALFALFA 15 [hp_X]/1 mL; FRAXINUS AMERICANA BARK 15 [hp_X]/1 mL; QUERCUS ROBUR NUT 15 [hp_X]/1 mL; BERBERIS VULGARIS ROOT BARK 15 [hp_X]/1 mL; ACONITUM NAPELLUS 15 [hp_X]/1 mL; ARUNDO PLINIANA ROOT 15 [hp_X]/1 mL; DYSPHANIA AMBROSIOIDES 15 [hp_X]/1 mL; HELIANTHEMUM CANADENSE 15 [hp_X]/1 mL; DROSERA ANGLICA 15 [hp_X]/1 mL; SOLANUM DULCAMARA TOP 15 [hp_X]/1 mL; RHODODENDRON TOMENTOSUM LEAFY TWIG 15 [hp_X]/1 mL; ONOSMODIUM VIRGINIANUM 15 [hp_X]/1 mL; POPULUS BALSAMIFERA LEAF BUD 15 [hp_X]/1 mL; POPULUS TREMULOIDES LEAF 15 [hp_X]/1 mL; ANEMONE PULSATILLA 15 [hp_X]/1 mL; SANGUINARIA CANADENSIS ROOT 15 [hp_X]/1 mL; DATURA STRAMONIUM 15 [hp_X]/1 mL; ELYMUS REPENS ROOT 15 [hp_X]/1 mL; URTICA URENS 15 [hp_X]/1 mL; WYETHIA HELENIOIDES ROOT 15 [hp_X]/1 mL; ONION 15 [hp_X]/1 mL; AMBROSIA ARTEMISIIFOLIA 15 [hp_X]/1 mL; AMMONIUM CARBONATE 15 [hp_X]/1 mL; ARALIA RACEMOSA ROOT 15 [hp_X]/1 mL; ARSENIC TRIOXIDE 15 [hp_X]/1 mL; ARTEMISIA VULGARIS ROOT 15 [hp_X]/1 mL; BELLIS PERENNIS 15 [hp_X]/1 mL; BRYONIA ALBA ROOT 15 [hp_X]/1 mL; CHELIDONIUM MAJUS 15 [hp_X]/1 mL; CALCIUM SULFIDE 15 [hp_X]/1 mL; EUPATORIUM PERFOLIATUM FLOWERING TOP 15 [hp_X]/1 mL; EUPHRASIA STRICTA 15 [hp_X]/1 mL; GELSEMIUM SEMPERVIRENS ROOT 15 [hp_X]/1 mL; HISTAMINE DIHYDROCHLORIDE 15 [hp_X]/1 mL; POTASSIUM DICHROMATE 15 [hp_X]/1 mL; POTASSIUM IODIDE 15 [hp_X]/1 mL; LACHESIS MUTA VENOM 15 [hp_X]/1 mL; LYCOPODIUM CLAVATUM SPORE 15 [hp_X]/1 mL; SODIUM CHLORIDE 15 [hp_X]/1 mL; SCHOENOCAULON OFFICINALE SEED 15 [hp_X]/1 mL; SOLIDAGO VIRGAUREA FLOWERING TOP 15 [hp_X]/1 mL; TRILLIUM ERECTUM ROOT 15 [hp_X]/1 mL; GOLDENSEAL 6 [hp_X]/1 mL; USTILAGO MAYDIS 15 [hp_X]/1 mL; APIS MELLIFERA 6 [hp_X]/1 mL; ECHINACEA, UNSPECIFIED 6 [hp_X]/1 mL; TARAXACUM OFFICINALE 6 [hp_X]/1 mL; PARTHENIUM HYSTEROPHORUS 16 [hp_X]/1 mL; ROSA X DAMASCENA FLOWERING TOP 15 [hp_X]/1 mL
INACTIVE INGREDIENTS: ALCOHOL; WATER

Hay 4834L

INDICATIONS & USAGE SECTION

Formulated for associated symptoms of late Summer and Fall pollens such as nasal catarrh, post-nasal drip, sneezing, glandular swellings and pharyngitis.

DOSAGE & ADMINISTRATION SECTION

Directions: Ages 12 and up, take 6 drops by mouth (ages 0 to 11, give 3 drops) as needed or as directed by a health professional.

OTC - ACTIVE INGREDIENT SECTION

Equal parts of Apis mellifica 6x, Echinacea 6x, Hydrastis canadensis 6x, Taraxacum officinale 6x, Aconitum napellus 15x, Alfalfa 15x, Allium cepa 15x, Ambrosia artemisiaefolia 15x, Ammonium carbonicum 15x, Aralia racemosa 15x, Arsenicum album 15x, Artemisia vulgaris 15x, Arundo mauritanica 15x, Bellis perennis 15x, Berberis vulgaris 15x, Bryonia 15x, Calluna vulgaris, flos 15x, Chelidonium majus 15x, Chenopodium anthelminticum 15x, Cistus canadensis 15x, Drosera 15x, Dulcamara 15x, Eupatorium perfoliatum 15x, Euphrasia officinalis 15x, Fagus sylvatica 15x, Fraxinus americana 15x, Gelsemium sempervirens 15x, Hepar sulphuris calcareum 15x, Histaminum hydrochloricum 15x, Kali bichromicum 15x, Kali iodatum 15x, Lachesis mutus 15x, Ledum palustre 15x, Lillium tigrinum 15x, Lycopodium clavatum 15x, Natrum muriaticum 15x, Onosmodium virginianum 15x, Populus candicans 15x, Populus tremuloides 15x, Pulsatilla 15x, Quercus glandium spiritus 15x, Rosa damascena 15x, Sabadilla 15x, Salix nigra 15x, Sanguinaria canadensis 15x, Solidago virgaurea 15x, Stramonium 15x, Trillium pendulum 15x, Triticum repens 15x, Urtica urens 15x, Ustilago maidis 15x, Wyethia helenoides 15x, Xerophyllum asphodeloides 15x, Parthenium 16x, Ulmus fulva 16x.

OTC - PURPOSE SECTION

Formulated for associated symptoms of late Summer and Fall pollens such as nasal catarrh, post-nasal drip, sneezing, glandular swellings and pharyngitis.

INACTIVE INGREDIENT SECTION

Inactive Ingredients: USP Purified Water; USP Gluten-free, non-GMO, organic cane alcohol 20%.

QUESTIONS SECTION

newtonlabs.net – Questions? 800.448.7256

Newton Laboratories, Inc. FDA Est # 1051203 - Conyers, GA 30013

WARNINGS SECTION

WARNINGS: Keep out of reach of children. Do not use if tamper-evident seal is broken or missing. If symptoms worsen or persist for more than a few days, consult a doctor. If pregnant or breast-feeding, ask a doctor before use.

OTC - PREGNANCY OR BREAST FEEDING SECTION

If pregnant or breast-feeding, ask a doctor before use.

OTC - KEEP OUT OF REACH OF CHILDREN SECTION

Keep out of reach of children.